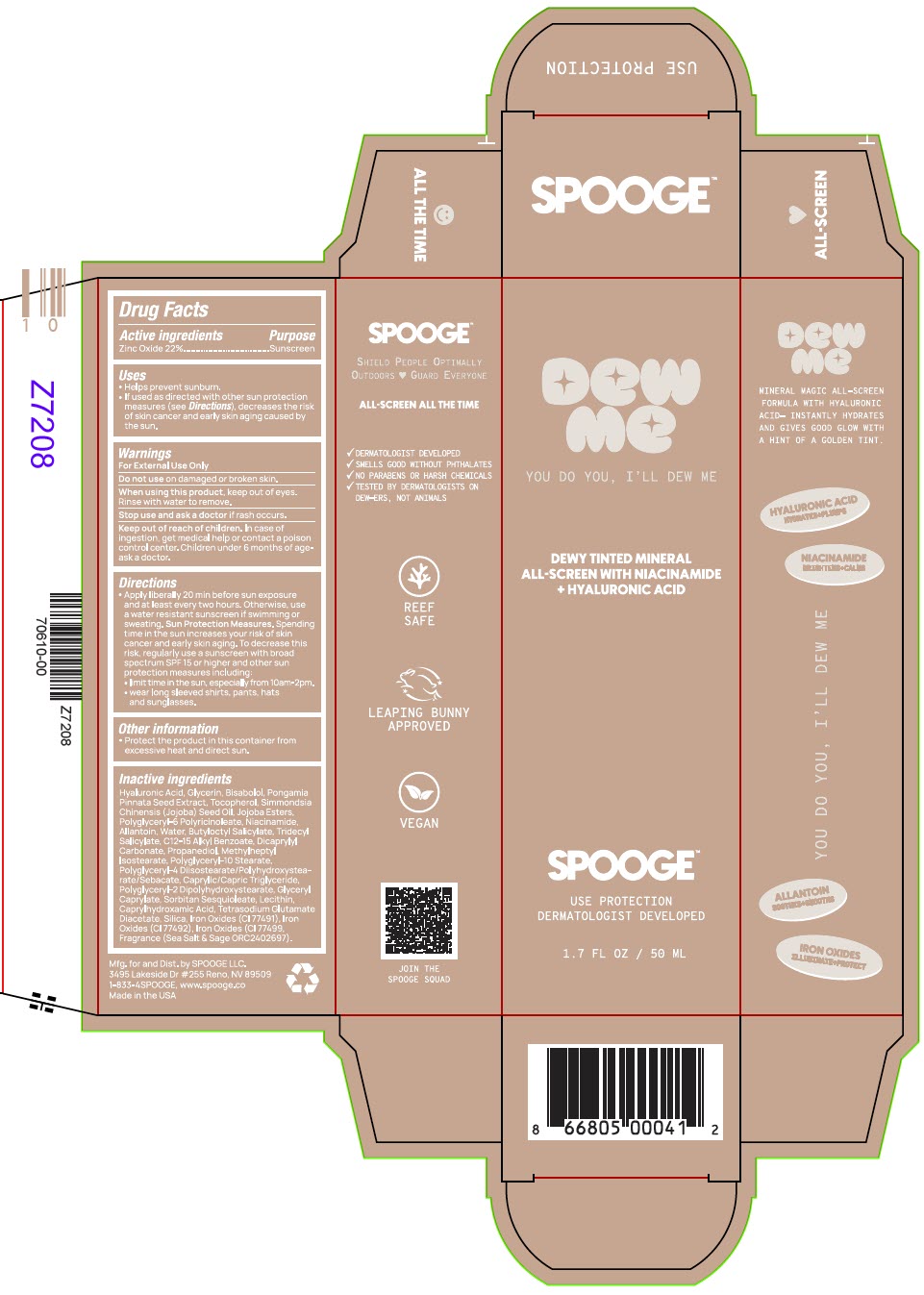 DRUG LABEL: Dew Me
NDC: 85385-135 | Form: LOTION
Manufacturer: Spooge
Category: otc | Type: HUMAN OTC DRUG LABEL
Date: 20250626

ACTIVE INGREDIENTS: Zinc Oxide 22 g/100 mL
INACTIVE INGREDIENTS: Hyaluronic Acid; Glycerin; LEVOMENOL; PONGAMIA PINNATA SEED; Tocopherol; JOJOBA OIL; POLYGLYCERYL-6 POLYRICINOLEATE; Niacinamide; Allantoin; Water; Butyloctyl Salicylate; TRIDECYL SALICYLATE; ALKYL (C12-15) BENZOATE; Dicaprylyl Carbonate; Propanediol; METHYLHEPTYL ISOSTEARATE; Polyglyceryl-10 Stearate; POLYGLYCERYL-4 DIISOSTEARATE/POLYHYDROXYSTEARATE/SEBACATE; MEDIUM-CHAIN TRIGLYCERIDES; POLYGLYCERYL-2 DIPOLYHYDROXYSTEARATE; GLYCERYL MONOCAPRYLATE; SORBITAN SESQUIOLEATE; CAPRYLHYDROXAMIC ACID; TETRASODIUM GLUTAMATE DIACETATE; SILICON DIOXIDE; FERRIC OXIDE RED; FERRIC OXIDE YELLOW; FERROSOFERRIC OXIDE

Dew Me

Drug Facts

Active ingredients

Zinc Oxide 22%.

Purpose

Sunscreen

Uses

* Helps prevent sunburn.

« If used as directed with other sun protection measures (see Directions), decreases the risk of skin cancer and early skin aging caused by the sun.

Warnings

For External Use Only

Do not use on damaged or broken skin.

When using this product, keep out of eyes. Rinse with water to remove.

Stop use and ask a doctor if rash occurs.

Keep out of reach of children. In case of ingestion, get medical help or contact a poison control center. Children under 6 months of age- ask a doctor.

Directions

+ Apply liberally 20 min before sun exposure and at least every two hours. Otherwise, use a water resistant sunscreen if swimming or sweating. Sun Protection Measures. Spending time in the sun increases your risk of skin cancer and early skin aging. To decrease this risk, regularly use a sunscreen with broad spectrum SPF 15 or higher and other sun protection measures including:

+ limit time in the sun, especially from 10am-2pm.

* wear long sleeved shirts, pants, hats and sunglasses.

Other information

* Protect the product in this container from excessive heat and direct sun.

Inactive ingredients

Hyaluronic Acid, Glycerin, Bisabolol, Pongamia Pinnata Seed Extract, Tocopherol, Simmondsia Chinensis (Jojoba) Seed Oil, Jojoba Esters, Polyglyceryl-6 Polyricinoleate, Niacinamide, Allantoin, Water, Butyloctyl Salicylate, Tridecy| Salicylate, C12-15 Alkyl Benzoate, Dicaprylyl Carbonate, Propanediol, Methyihepty! Isostearate, Polyglyceryl-10 Stearate, Polyglyceryl-4 Diisostearate/Polyhydroxysteatate/Sebacate, Caprylic/Capric Triglyceride, Polyglyceryl-2 Dipolyhydroxystearate, Glyceryl Caprylate, Sorbitan Sesquioleate, Lecithin, Caprylhydroxamic Acid, Tetrasodium Glutamate Diacetate, Silica, Iron Oxides (CI 77491), Iron Oxides (C! 77492), Iron Oxides (CI77499, Fragrance (Sea Salt & Sage ORC2402697).

Dist. by SPOOGE LLC.
3495 Lakeside Dr #255 Reno, NV 89509

PRINCIPAL DISPLAY PANEL - 50 ML Tube Box

DEW
ME

YOU DO YOU, I'LL DEW ME

DEWY TINTED MINERAL
ALL-SCREEN WITH NIACINAMIDE
+ HYALURONIC ACID

SPOOGE™

USE PROTECTION
DERMATOLOGIST DEVELOPED

1.7 FL OZ / 50 ML